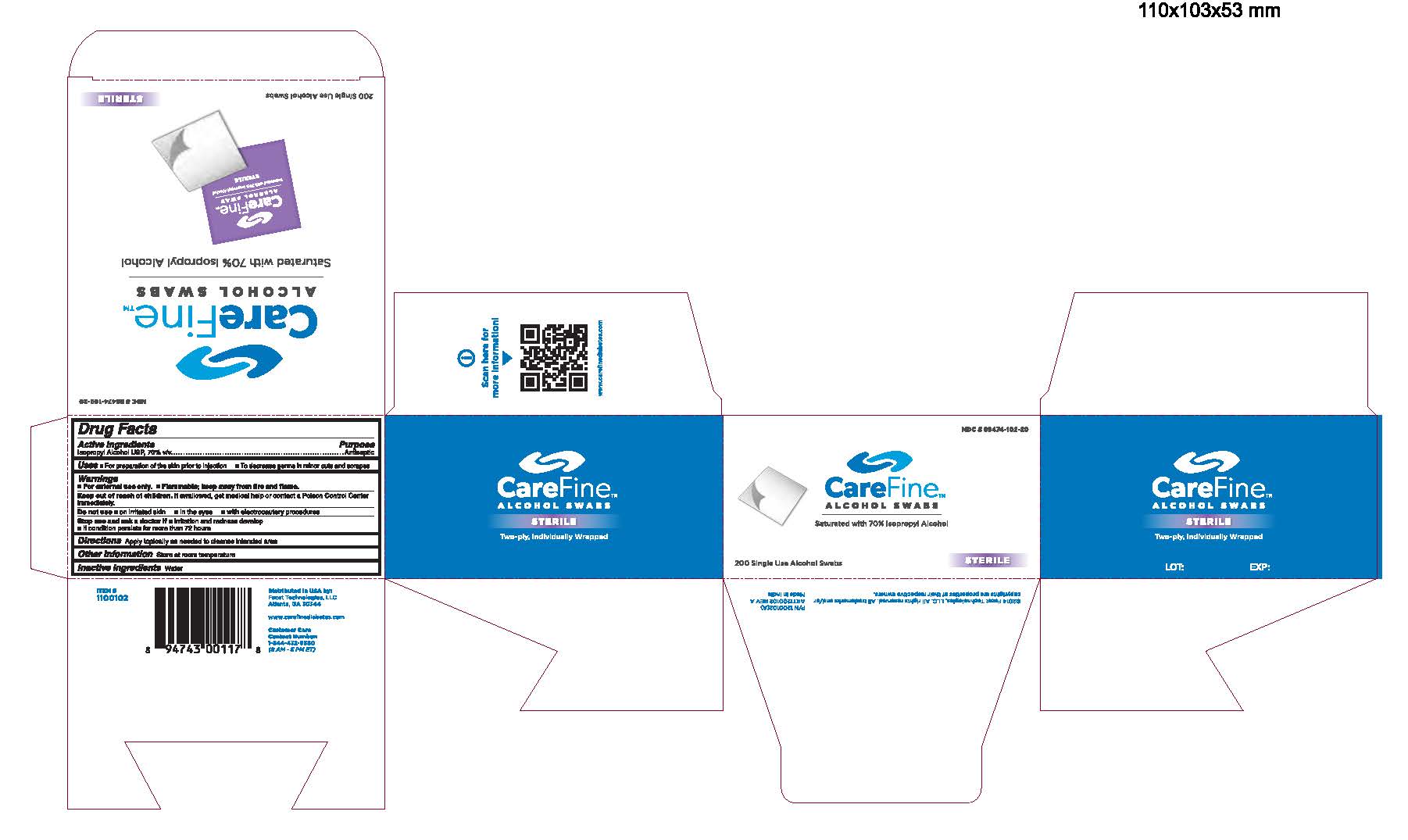 DRUG LABEL: CareFine Alcohol Swabs 200 Ct
NDC: 89474-102 | Form: SWAB
Manufacturer: Facet Technologies
Category: otc | Type: HUMAN OTC DRUG LABEL
Date: 20141107

ACTIVE INGREDIENTS: Isopropyl Alcohol 70 mL/100 mL
INACTIVE INGREDIENTS: Water

Active Ingredients

Isopropyl Alcohol USP, 70% v/v

Purpose

Antiseptic

Uses

• For preparation of the skin prior to injection

• To decrease germs in minor cuts and scrapes

Warnings

- For external use only
- Flammable, keep away from fire and flame

Keep out of reach of children.

If swallowed, get medical help or contact a Poison Control Center immediately.

Do not use

- on irritated skin
- in the eyes
- with electrocautery procedures

Stop use and ask a doctor if

- irritation and redness develop
- if condition persists for more than 72 hours

Directions

Apply topically as needed to cleanse intended area

Other information

Store at room temperature

Inactive Ingredients

Water

CareFine Alcohol Swabs 200 ct.

CareFineTM Alcohol Swabs

NDC # 89474-102-20

Saturated with 70% Isopropyl Alcohol

200 Single Use Alcohol Swabs

Sterile

1100102 CF 200ct Swabs ART1200102A.jpg